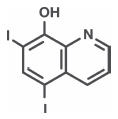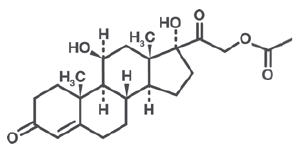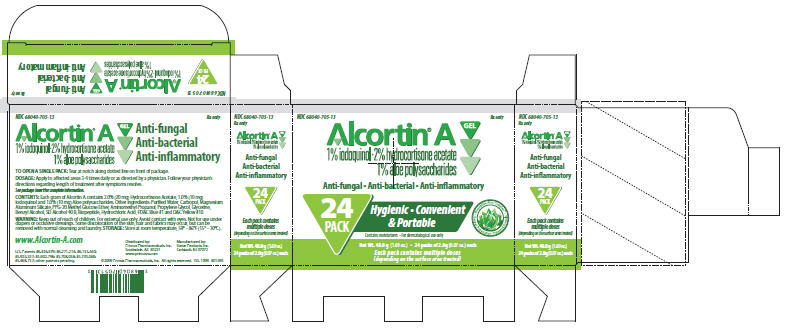 DRUG LABEL: Alcortin A
NDC: 68040-705 | Form: GEL
Manufacturer: Primus Pharmaceuticals
Category: prescription | Type: HUMAN PRESCRIPTION DRUG LABEL
Date: 20091030

ACTIVE INGREDIENTS: HYDROCORTISONE ACETATE 20 mg/1 g; ALOE VERA LEAF 10 mg/1 g; Iodoquinol 10 mg/1 g

ALCORTIN® A gel

Prescribing Information

DESCRIPTION

Each gram of Alcortin® A contains 2.0% (20 mg) Hydrocortisone Acetate and 1.0% (10 mg) Iodoquinol. Also contains 1.0% (10 mg) Aloe polysaccharide [U.S. Patents #6,436,679; #6,271,214; #6,133,440; #5,708,038; patent pending] . Other ingredients: Purified Water, Carbopol, Magnesium Aluminum Silicate, PPG-20 Methyl Glucose Ether, Aminomethyl Propanol, Propylene Glycol, Glycerine, Benzyl Alcohol, SD Alcohol 40 B, Biopeptide, Hydrochloric Acid, FD&C Blue # 1 and FD&C Yellow # 10.

Iodoquinol

Iodoquinol is an antifungal and antibacterial agent. Chemically, Iodoquinol is [5,7-diiodo-8-quinolinol] with the molecular formula (C9H5I2NO) and is represented by the following structural formula:

Hydrocortisone Acetate

Hydrocortisone acetate is an anti-inflammatory and antipruritic agent. Chemically, hydrocortisone acetate is [Pregn-4-ene-3, 20-dione, 11, 17, 21- trihydroxy-, (11β)-] with the molecular formula (C21H30O5) and is represented by the following structural formula:

CLINICAL PHARMACOLOGY

Hydrocortisone Acetate has anti-inflammatory, antipruritic and vasoconstrictive properties. While the mechanism of anti-inflammatory activity is unclear, there is evidence to suggest that a recognizable correlation exists between vasoconstrictor potency and therapeutic efficacy in humans. Iodoquinol has both antifungal and antibacterial properties.

Pharmacokinetics

The extent of percutaneous absorption of topical steroids is determined by many factors including the vehicle, the integrity of the epidermal barrier and the use of occlusive dressings. Hydrocortisone acetate can be absorbed from normal intact skin. Inflammation and/or other inflammatory disease processes in the skin increase percutaneous absorption. Occlusive dressings substantially increase the percutaneous absorption of topical corticosteroids. Once absorbed through the skin, hydrocortisone acetate is metabolized in the liver and most body tissue to hydrogenated and degraded forms such as tetrahydrocortisone and tetrahydrocortisol. These are excreted in the urine, mainly conjugated as glucuronides, together with a very small proportion of unchanged hydrocortisone acetate. There are no data available regarding the percutaneous absorption of iodoquinol; however, following oral administration, 3-5% of the dose was recovered in the urine as a glucuronide.

INDICATIONS AND USAGE

Based on a review of a related drug by the National Research Council and subsequent FDA classification for that drug, the indications are as follows: "Possibly" Effective: Contact or atopic dermatitis; impetiginized eczema; nummular eczema; endogenous chronic infectious dermatitis; stasis dermatitis; pyoderma; nuchal eczema and chronic eczematoid otitis externa; acne urticata; localized or disseminated neurodermatitis; lichen simplex chronicus; anogenital pruritus (vulvae, scroti, ani); folliculitis; bacterial dermatoses; mycotic dermatoses such as tinea (capitis, cruris, corporis, pedis); monliasis; intertrigo. Final classification of the less-than-effective indications requires further investigation.

CONTRAINDICATIONS

Alcortin A is contraindicated in those patients with a history of hypersensitivity to hydrocortisone acetate, iodoquinol, aloe vera, glycine, histidine, lysine, palmitic acid or any other components of the preparation.

WARNINGS AND PRECAUTIONS

For external use only. Keep away from eyes. If irritation develops, the use of Alcortin A should be discontinued and appropriate therapy instituted. Staining of the skin, hair and fabrics may occur. Not intended for use on infants or under diapers or occlusive dressings. If extensive areas are treated or if the occlusive dressing technique is used, the possibility exists of increased systemic absorption of the corticosteroid, and suitable precautions should be taken. Children may absorb proportionally larger amounts of topical corticosteroids and thus be more susceptible to systemic toxicity. Parents of pediatric patients should be advised not to use tight-fitting diapers or plastic pants on a child being treated in the diaper area, as these garments may constitute occlusive dressings. Iodoquinol may be absorbed through the skin and interfere with thyroid function tests. If such tests are contemplated, wait at least one month after discontinuance of therapy to perform these tests. The ferric chloride test for phenylketonuria (PKU) can yield a false positive result if iodoquinol is present in the diaper or urine. Prolonged use may result in overgrowth of non-susceptible organisms requiring appropriate therapy. Keep out of reach of children. Burning, itching, irritation and dryness have been reported infrequently following the use of topical corticosteroids.

Carcinogenesis, Mutagenisis and Impairment of Fertility

Long term animal studies have not been performed to evaluate the carcinogenic potential of the effect on fertility of hydrocortisone or iodoquinol. In vitro studies to determine mutagenicity with hydrocortisone have revealed negative results. Mutagenicity studies have not been performed with iodoquinol.

PREGNANCY

Pregnancy Category C

Animal reproductive studies have not been conducted with Alcortin A. It is not known whether Alcortin A can cause fetal harm when administered to pregnant women or can affect reproductive capacity. Alcortin A should be given to pregnant women only if clearly needed.

Nursing Mothers

It is not known whether this drug is excreted in human milk. Because many drugs are excreted in human milk, caution should be exercised when Alcortin A is administered to a nursing woman.

Pediatric Use

Safety and effectiveness in pediatric patients under the age of 12 have not been established.

ADVERSE REACTIONS

The following local adverse reactions are reported infrequently with topical corticosteroids. These reactions are listed in an approximate decreasing order of occurrence. Burning, itching, irritation, dryness, folliculitis, hypertrichosis, acneiform eruptions, hypopigmentation, perioral dermatitis, allergic contact dermatitis, maceration of the skin, secondary infections, skin atrophy, striae and miliaria.

DOSAGE AND ADMINISTRATION

Apply to affected area 3-4 times daily in accordance with physician's directions or as directed otherwise by a physician.

HOW SUPPLIED

FORM

48.0 gram carton of 24-count of 2.0 gram gel individual packs

NDC #68040-705-13

2.0 gram gel individual pack

NDC # 68040-705-02

10 count carton of 2.0 gram gel sample packs - not for resale

NDC # 68040-705-08

Each 2.0 gram gel pack contains multiple doses depending on the surface area treated.

STORAGE

Store at room temperature 15º-30ºC (59º-86ºF).

Keep tightly closed.

Rx only
www.alcortin.com

Distributed by:
Primus Pharmaceuticals, Inc.
Scottsdale, AZ 85251
www.primusrx.com

Manufactured by:
Sonar Products, Inc.
Carlstadt, NJ 07072

© 2007 Primus Pharmaceuticals, Inc. All rights reserved.
ISS. 1207 #00499

PRINCIPAL DISPLAY PANEL - 24 Pack Carton

NDC 68040-705-13
Rx only

Alcortin® A Gel
1% iodoquinol•2% hydrocortisone acetate
1% aloe polysaccharides

Anti-fungal • Anti-bacterial • Anti-inflammatory

24
PACK

Hygienic • Convenient
& Portable

Contains moisturizers • For dermatological use only

Biopeptide Aloe Complex™
Deeper Penetration
Patented Formula

Net Wt. 48.0 g (1.69 oz.) • 24 packs of 2.0g (0.07 oz.) each

Each pack contains multiple doses
(depending on the surface area treated)